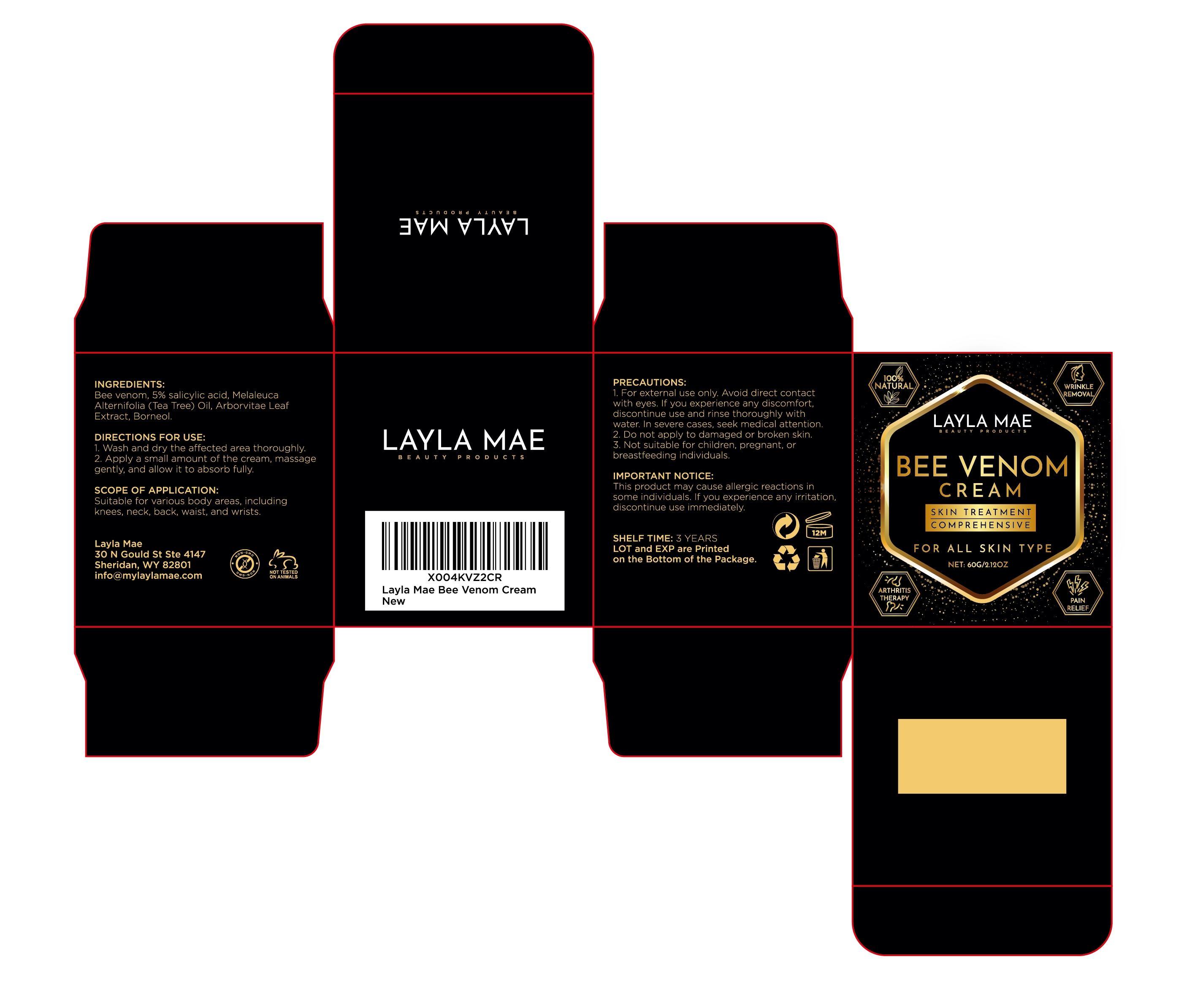 DRUG LABEL: BEE VENOM Cream
NDC: 85594-002 | Form: CREAM
Manufacturer: Dongguan Haiyi Cosmetics Co., Ltd.
Category: otc | Type: HUMAN OTC DRUG LABEL
Date: 20250506

ACTIVE INGREDIENTS: SALICYLIC ACID 5 mg/60 g
INACTIVE INGREDIENTS: APIS MELLIFERA VENOM; THUJA OCCIDENTALIS LEAFY TWIG; TEA TREE OIL; BORNEOL

85594-002-001 BEE VENOM Cream

ACTIVE INGREDIENT

5% Salicylic Acid

INACTIVE INGREDIENT

Bee Venom，Melaleuca Alternifolia (Tea Tree) Oil ，Arborvitae Leaf Extract，Borneol

PURPOSE

WRINKLE REMOVAL;PAIN RELIEF；ARTHRITIS THERAPY

WARNINGS

This product may cause allerglc reactlons in some individuals.lf you experience any irritation,discontinue use immediately

STOP USE

This product may cause alleralc reactlons in some individuals.f you experience any irritation,discontinue use immediately

Do not apply to damaged or broken skin.

Not suitable for children, pregnant, or breastfeeding individuals.

INDICATIONS AND USAGE

Suitable for various body areas, including
knees, neck, back, waist, and wrists.

DOSAGE AND ADMINISTRATION

take an appropriateamount,Use 2-3 times a week